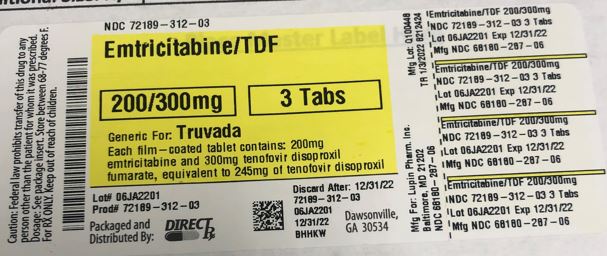 DRUG LABEL: EMTRICITABINE AND TENOFOVIR DISOPROXIL FUMARATE
NDC: 72189-312 | Form: TABLET, FILM COATED
Manufacturer: DirectRx
Category: prescription | Type: HUMAN PRESCRIPTION DRUG LABEL
Date: 20250121

ACTIVE INGREDIENTS: EMTRICITABINE 200 mg/1 1; TENOFOVIR DISOPROXIL FUMARATE 300 mg/1 1
INACTIVE INGREDIENTS: CELLULOSE, MICROCRYSTALLINE; CROSCARMELLOSE SODIUM; HYPROMELLOSE 2910 (6 MPA.S); MAGNESIUM STEARATE; LACTOSE MONOHYDRATE; SILICON DIOXIDE; TRIACETIN; MANNITOL; TITANIUM DIOXIDE

EMTRICITABINE AND TENOFOVIR DISOPROXIL FUMARATE

INDICATIONS AND USAGE

1.1 Treatment of HIV-1 Infection

Emtricitabine and tenofovir disoproxil fumarate tablets are indicated in combination with other antiretroviral agents for the treatment of HIV-1 infection in adults and pediatric patients weighing at least 17 kg [see Clinical Studies (14)].

1.2 HIV-1 Pre-Exposure Prophylaxis (PrEP)

Emtricitabine and tenofovir disoproxil fumarate tablets are indicated in at – risk adults and adolescents weighing at least 35 kg for pre-exposure prophylaxis (PrEP) to reduce the risk of sexually acquired HIV-1 infection. Individuals must have a negative HIV-1 test immediately prior to initiating emtricitabine and tenofovir disoproxil fumarate tablets for HIV-1 PrEP [see Dosage and Administration (2.2), Warnings and Precautions (5.2)].

DOSAGE AND ADMINISTRATION

2.1 Testing Prior to Initiation of Emtricitabine and Tenofovir Disoproxil Fumarate Tablets for Treatment of HIV-1 Infection or for HIV-1 PrEP

Prior to or when initiating emtricitabine and tenofovir disoproxil fumarate tablets, test individuals for hepatitis B virus infection [see Warnings and Precautions (5.1)].

Prior to initiation and during use of emtricitabine and tenofovir disoproxil fumarate tablets, on a clinically appropriate schedule, assess serum creatinine, estimated creatinine clearance, urine glucose and urine protein in all individuals. In individuals with chronic kidney disease, also assess serum phosphorus [see Warnings and Precautions (5.3)].

2.2 HIV-1 Screening for Individuals Receiving Emtricitabine and Tenofovir Disoproxil Fumarate Tablets for HIV-1 PrEP

Screen all individual for HIV-1 infection immediately prior to initiating emtricitabine and tenofovir disoproxil fumarate tablets for HIV-1 PrEP and at least once every 3 months while taking emtricitabine and tenofovir disoproxil fumarate tablets, and upon diagnosis of any other sexually transmitted infections (STIs) [see Indications and Usage (1.2), Contraindications (4) and Warnings and Precautions (5.2)].

If recent (<1 month) exposures to HIV-1 are suspected or clinical symptoms consistent with acute HIV-1 infection are present, use a test approved or cleared by the FDA as an aid in the diagnosis of acute or primary HIV-1 infection [see Warnings and Precautions (5.2), Use in Specific Populations (8.4), and Clinical Studies (14.3 and 14.4)].

2.3 Recommended Dosage for Treatment of HIV-1 Infection in Adults and Pediatric Patients Weighing at Least 35 kg

Emtricitabine and tenofovir disoproxil fumarate tablet is a two-drug fixed dose combination product containing emtricitabine (FTC) and tenofovir disoproxil fumarate (TDF). The recommended dosage of emtricitabine and tenofovir disoproxil fumarate tablets in adults and in pediatric patients weighing at least 35 kg is one tablet (containing 200 mg of FTC and 300 mg of TDF) once daily taken orally with or without food [see Clinical Pharmacology (12.3)].

2.5 Recommended Dosage for HIV-1 PrEP in Adults and Adolescents Weighing at Least 35 kg

The dosage of emtricitabine and tenofovir disoproxil fumarate tablets for HIV-1 PrEP is one tablet (containing 200 mg of FTC and 300 mg of TDF) once daily taken orally with or without food in HIV-1 uninfected adults and adolescents weighing at least 35 kg [see Clinical Pharmacology (12.3)].

2.6 Dosage Adjustment in Individuals with Renal Impairment

Treatment of HIV-1 Infection

Table 2 provides dosage interval adjustment for patients with renal impairment. No dosage adjustment is necessary for HIV-1 infected patients with mild renal impairment (creatinine clearance 50 to 80 mL/min). The safety and effectiveness of the dosing interval adjustment recommendations in patients with moderate renal impairment (creatinine clearance 30 to 49 mL/min) have not been clinically evaluated; therefore, clinical response to treatment and renal function should be closely monitored in these patients [see Warnings and Precautions (5.3)].

No data are available to make dosage recommendations in pediatric patients with renal impairment.

Table 2 Dosage Interval Adjustment for HIV-1 Infected Adult Patients with Altered Creatinine Clearance

a.Calculated using ideal (lean) body weight

Creatinine Clearance (mL/min)a
50
30 to 49
<30
(Including Patients Requiring Hemodialysis)
Recommended Dosing Interval
Every 24 hours
Every 48 hours
Emtricitabine and tenofovir disoproxil fumarate tablets are not recommended.

HIV-1 PrEP

Emtricitabine and tenofovir disoproxil fumarate tablets for HIV-1 PrEP are not recommended in HIV-1 uninfected individuals with estimated creatinine clearance below 60 mL/min [see Warnings and Precautions (5.3)].

If a decrease in estimated creatinine clearance is observed in uninfected individuals while using emtricitabine and tenofovir disoproxil fumarate tablets for HIV-1 PrEP, evaluate potential causes and re-assess potential risks and benefits of continued use [see Warnings and Precautions (5.3)]

DOSAGE FORMS AND STRENGTHS

Emtricitabine and tenofovir disoproxil fumarate tablets are available in one dose strength.

200 mg/300 mg Tablets: 200 mg of FTC and 300 mg of TDF (equivalent to 245 mg of tenofovir disoproxil): white, capsule shaped, biconvex film-coated, debossed with "LU" on one side and "Q31" on the other side.

CONTRAINDICATIONS

Emtricitabine and tenofovir disoproxil fumarate tablets for HIV-1 PrEP are contraindicated in individuals with unknown or positive HIV-1 status [see Warnings and Precautions (5.2)].

WARNINGS AND PRECAUTIONS

5.1 Severe Acute Exacerbation of Hepatitis B in Individuals with HBV Infection

All individuals should be tested for the presence of chronic hepatitis B virus (HBV) before or when initiating emtricitabine and tenofovir disoproxil fumarate tablets [see Dosage and Administration (2.1)].

Severe acute exacerbations of hepatitis B (e.g., liver decompensation and liver failure) have been reported in HBV-infected individuals who have discontinued emtricitabine and tenofovir disoproxil fumarate tablets. Individuals infected with HBV who discontinue emtricitabine and tenofovir disoproxil fumarate tablets should be closely monitored with both clinical and laboratory follow-up for at least several months after stopping treatment. If appropriate, anti-hepatitis B therapy may be warranted, especially in individuals with advanced liver disease or cirrhosis, since posttreatment exacerbation of hepatitis may lead to hepatic decompensation and liver failure. HBV-uninfected individuals should be offered vaccination.

5.2 Comprehensive Management to Reduce the Risk of Sexually Transmitted Infections, Including HIV-1 and Development of HIV-1 Resistance When Emtricitabine and Tenofovir Disoproxil Fumarate Tablets are Used for HIV-1 PrEP

Use emtricitabine and tenofovir disoproxil fumarate tablets for HIV-1 PrEP to reduce the risk of HIV-1 infection as part of a comprehensive prevention strategy that includes other prevention measures, including adherence to daily administration and safer sex practices, including condoms, to reduce the risk of sexually transmitted infections (STIs). The time from initiation of emtricitabine and tenofovir disoproxil fumarate tablets for HIV-1 PrEP to maximal protection against HIV-1 infection is unknown.

Risk of HIV-1 acquisition includes behavioral, biological, or epidemiologic factors including but not limited to condomless sex, past or current STIs, self-identified HIV risk, having sexual partners of unknown HIV-1 viremic status, or sexual activity in a high prevalence area or network.

Counsel individuals on the use of other prevention measures (e.g., consistent and correct condom use, knowledge of partner(s)'HIV-1 status, including viral suppression status, regular testing for STIs that can facilitate HIV-1 transmission. Inform uninfected individuals about and support their efforts in reducing sexual risk behavior.

Use emtricitabine and tenofovir disoproxil fumarate tablets to reduce the risk of acquiring HIV-1 only in individuals confirmed to be HIV-negative. HIV-1 resistance substitutions may emerge in individuals with undetected HIV-1 infection who are taking only emtricitabine and tenofovir disoproxil fumarate tablets, because emtricitabine and tenofovir disoproxil fumarate tablets alone does not constitute a complete regimen for HIV-1 treatment [see Microbiology (12.4)]; therefore, care should be taken to minimize the risk of initiating or continuing emtricitabine and tenofovir disoproxil fumarate tablets before confirming the individual is HIV-1 negative.

Some HIV-1 tests, only detect anti-HIV antibodies and may not identify HIV-1 during the acute stage of infection. Prior to initiating emtricitabine and tenofovir disoproxil fumarate tablets for HIV-1 PrEP, ask seronegative individuals about recent (in past month) potential exposure events (e.g., condomless sex or condom breaking during sex with a partner of unknown HIV-1 status or unknown viremic status, or a recent STI), and evaluate for current or recent signs or symptoms consistent with acute HIV-1 infection (e.g., fever, fatigue, myalgia, skin rash).
If recent (<1 month) exposures to HIV-1 are suspected or clinical symptoms consistent with acute HIV-1 infection are present, use a test approved or cleared by the FDA as an aid in the diagnosis of acute or primary HIV-1 infection.

While using emtricitabine and tenofovir disoproxil fumarate tablets for HIV-1 PrEP, HIV-1 testing should be repeated at least every 3 months, and upon diagnosis of any other STIs.

If an HIV-1 test indicates possible HIV-1 infection, or if symptoms consistent with acute HIV-1 infection develop following a potential exposure event, convert the HIV-1 PrEP regimen to an HIV treatment regimen until negative infection status is confirmed using a test approved or cleared by the FDA as an aid in the diagnosis of acute or primary HIV-1 infection.

Counsel HIV-1 uninfected individuals to strictly adhere to the once daily emtricitabine and tenofovir disoproxil fumarate tablets dosing schedule. The effectiveness of emtricitabine and tenofovir disoproxil fumarate tablets in reducing the risk of acquiring HIV-1 is strongly correlated with adherence, as demonstrated by measurable drug levels in clinical trials of emtricitabine and tenofovir disoproxil fumarate tablets for HIV-1 PrEP Some individuals, such as adolescents, may benefit from more frequent visits and counseling to support adherence [see Use in Specific Populations (8.4), Microbiology (12.4), and Clinical Studies (14.3 and 14.4)].

5.3 New Onset or Worsening Renal Impairment

Emtricitabine and tenofovir are principally eliminated by the kidney. Renal impairment, including cases of acute renal failure and Fanconi syndrome (renal tubular injury with severe hypophosphatemia), has been reported with the use of TDF, a component of emtricitabine and tenofovir disoproxil fumarate tablets [see Adverse Reactions (6.2)].

Prior to initiation and during use of emtricitabine and tenofovir disoproxil fumarate tablets, on a clinically appropriate schedule, assess serum creatinine, estimated creatinine clearance, urine glucose, and urine protein in all individuals. In individuals with chronic kidney disease, also assess serum phosphorus.

Emtricitabine and tenofovir disoproxil fumarate tablets should be avoided with concurrent or recent use of a nephrotoxic agent (e.g., high-dose or multiple non-steroidal anti-inflammatory drugs [NSAIDs]) [see Drug Interactions (7.1)]. Cases of acute renal failure after initiation of high-dose or multiple NSAIDs have been reported in HIV-infected patients with risk factors for renal dysfunction who appeared stable on TDF. Some patients required hospitalization and renal replacement therapy. Alternatives to NSAIDs should be considered, if needed, in individuals at risk for renal dysfunction.

Persistent or worsening bone pain, pain in extremities, fractures, and/or muscular pain or weakness may be manifestations of proximal renal tubulopathy and should prompt an evaluation of renal function in individuals at risk of renal dysfunction.

Treatment of HIV-1 Infection

Dosing interval adjustment of emtricitabine and tenofovir disoproxil fumarate tablets and close monitoring of renal function are recommended in all patients with estimated creatinine clearance 30 to 49 mL/min [see Dosage and Administration (2.6)]. No safety or efficacy data are available in patients with renal impairment who received emtricitabine and tenofovir disoproxil fumarate using these dosing guidelines, so the potential benefit of emtricitabine and tenofovir disoproxil fumarate tablets therapy should be assessed against the potential risk of renal toxicity. Emtricitabine and tenofovir disoproxil fumarate tablets are not recommended in patients with estimated creatinine clearance below 30 mL/min or patients requiring hemodialysis.

HIV-1 PrEP

Emtricitabine and tenofovir disoproxil fumarate tablets for HIV-1 PrEP are not recommended in uninfected individuals with estimated creatinine clearance less than 60 mL/min. If a decrease in estimated creatinine clearance is observed while using emtricitabine and tenofovir disoproxil fumarate tablets for HIV-1 PrEP, evaluate potential causes and re-assess potential risks and benefits of continued use [see Dosage and Administration (2.6)].

5.4 Immune Reconstitution Syndrome

Immune reconstitution syndrome has been reported in HIV-1 infected patients treated with combination antiretroviral therapy, including emtricitabine and tenofovir disoproxil fumarate tablets. During the initial phase of combination antiretroviral treatment, HIV-1 infected patients whose immune system responds may develop an inflammatory response to indolent or residual opportunistic infections (such as Mycobacterium avium infection, cytomegalovirus, Pneumocystis jirovecii pneumonia [PCP], or tuberculosis), which may necessitate further evaluation and treatment.

Autoimmune disorders (such as Graves' disease, polymyositis, Guillain-Barr¡SR syndrome and autoimmune hepatitis) have also been reported to occur in the setting of immune reconstitution; however, the time to onset is more variable and can occur many months after initiation of treatment.

5.5 Bone Loss and Mineralization Defects

Bone Mineral Density

In clinical trials in HIV-1 infected adults and in a clinical trial of HIV-1 uninfected individuals, TDF (a component of emtricitabine and tenofovir disoproxil fumarate tablets) was associated with slightly greater decreases in bone mineral density (BMD) and increases in biochemical markers of bone metabolism, suggesting increased bone turnover relative to comparators [see Adverse Reactions (6.1)]. Serum parathyroid hormone levels and 1,25 Vitamin D levels were also higher in subjects receiving TDF.

Clinical trials evaluating TDF in pediatric and adolescent subjects were conducted. Under normal circumstances, BMD increases rapidly in pediatric patients. In HIV-1 infected subjects aged 2 years to less than 18 years, bone effects were similar to those observed in adult subjects and suggest increased bone turnover. Total body BMD gain was less in the TDF-treated HIV-1 infected pediatric subjects as compared to the control groups. Similar trends were observed in adolescent subjects aged 12 years to less than 18 years treated for chronic hepatitis B. In all pediatric trials, skeletal growth (height) appeared to be unaffected.

The effects of TDF-associated changes in BMD and biochemical markers on long-term bone health and future fracture risk are unknown. Assessment of BMD should be considered for adult and pediatric patients who have a history of pathologic bone fracture or other risk factors for osteoporosis or bone loss. Although the effect of supplementation with calcium and vitamin D was not studied, such supplementation may be beneficial. If bone abnormalities are suspected, appropriate consultation should be obtained.

Mineralization Defects

Cases of osteomalacia associated with proximal renal tubulopathy, manifested as bone pain or pain in extremities and which may contribute to fractures, have been reported in association with TDF use [see Adverse Reactions (6.1)]. Arthralgia and muscle pain or weakness have also been reported in cases of proximal renal tubulopathy. Hypophosphatemia and osteomalacia secondary to proximal renal tubulopathy should be considered in patients at risk of renal dysfunction who present with persistent or worsening bone or muscle symptoms while receiving TDF-containing products [see Warnings and Precautions (5.3)].

5.6 Lactic Acidosis/Severe Hepatomegaly with Steatosis

Lactic acidosis and severe hepatomegaly with steatosis, including fatal cases, have been reported with the use of nucleoside analogs, including FTC and TDF, components of emtricitabine and tenofovir disoproxil fumarate tablets, alone or in combination with other antiretrovirals. Treatment with emtricitabine and tenofovir disoproxil fumarate tablets should be suspended in any individual who develops clinical or laboratory findings suggestive of lactic acidosis or pronounced hepatotoxicity (which may include hepatomegaly and steatosis even in the absence of marked transaminase elevations).

5.7 Risk of Adverse Reactions Due to Drug Interactions

The concomitant use of emtricitabine and tenofovir disoproxil fumarate tablets and other drugs may result in known or potentially significant drug interactions, some of which may lead to possible clinically significant adverse reactions from greater exposures of concomitant drugs [see Drug Interactions (7.2)].

See Table 7 for steps to prevent or manage these possible and known significant drug interactions, including dosing recommendations. Consider the potential for drug interactions prior to and during therapy with emtricitabine and tenofovir disoproxil fumarate tablets; review concomitant medications during therapy with emtricitabine and tenofovir disoproxil fumarate tablets; and monitor for adverse reactions associated with the concomitant drugs.

ADVERSE REACTIONS

The following adverse reactions are discussed in other sections of the labeling:

Severe Acute Exacerbations of Hepatitis B in Patients with HBV Infection [see Warnings and Precautions (5.1)] .
New Onset or Worsening Renal Impairment [see Warnings and Precautions (5.3)] .
Immune Reconstitution Syndrome [see Warnings and Precautions (5.4)] .
Bone Loss and Mineralization Defects [see Warnings and Precautions (5.5)] .
Lactic Acidosis/Severe Hepatomegaly with Steatosis [see Warnings and Precautions (5.6)] .

6.1 Clinical Trials Experience

Because clinical trials are conducted under widely varying conditions, adverse reaction rates observed in the clinical trials of a drug cannot be directly compared to rates in the clinical trials of another drug and may not reflect the rates observed in practice.

Adverse Reactions from Clinical Trials Experience in HIV-1 Infected Subjects

Clinical Trials in Adult Subjects:

In Study 934, 511 antiretroviral-naïve subjects received efavirenz (EFV) administered in combination with either FTC+TDF (N=257) or zidovudine (AZT)/lamivudine (3TC) (N=254) for 144 weeks. The most common adverse reactions (incidence greater than or equal to 10%, all grades) included diarrhea, nausea, fatigue, headache, dizziness, depression, insomnia, abnormal dreams, and rash. Table 3 provides the treatment-emergent adverse reactions (Grades 2 to 4) occurring in greater than or equal to 5% of subjects treated in any treatment group.

Skin discoloration, manifested by hyperpigmentation, occurred in 3% of subjects taking FTC+TDF, and was generally mild and asymptomatic. The mechanism and clinical significance are unknown.

Table 3 Selected Adverse Reactionsa (Grades 2 to 4) Reported in 5% in Any Treatment Group in Study 934 (0 to 144 Weeks)

a.Frequencies of adverse reactions are based on all treatment-emergent adverse events, regardless of relationship to study drug.

b.From Weeks 96 to 144 of the trial, subjects received emtricitabine and tenofovir disoproxil fumarate tablets with efavirenz in place of FTC+TDF with efavirenz.

c.Rash event includes rash, exfoliative rash, rash generalized, rash macular, rash maculo-papular, rash pruritic, and rash vesicular.

FTC+TDF+EFVb
AZT/3TC+EFV
N=257
N=254
Fatigue
9%
8%
Depression
9%
7%
Nausea
9%
7%
Diarrhea
9%
5%
Dizziness
8%
7%
Upper respiratory tract infections
8%
5%
Sinusitis
8%
4%
Rash eventc
7%
9%
Headache
6%
5%
Insomnia
5%
7%
Nasopharyngitis
5%
3%
Vomiting
2%
5%

Laboratory Abnormalities: Laboratory abnormalities observed in this trial were generally consistent with those seen in other trials of TDF and/or FTC (Table 4).

Table 4 Significant Laboratory Abnormalities Reported in 1% of Subjects in Any Treatment Group in Study 934 (0 to 144 Weeks)

a.From Weeks 96 to 144 of the trial, subjects received emtricitabine and tenofovir disoproxil fumarate tablets with efavirenz in place of FTC+TDF with efavirenz.

FTC+TDF+EFVa
AZT/3TC+EFV
N=257
N=254
Any Grade 3 Laboratory Abnormality
30%
26%
Fasting Cholesterol (>240 mg/dL)
22%
24%
Creatine Kinase
(M: >990 U/L)
(F: >845 U/L)
9%
7%
Serum Amylase (>175 U/L)
8%
4%
Alkaline Phosphatase (>550 U/L)
1%
0%
AST
(M: >180 U/L)
(F: >170 U/L)
3%
3%
ALT
(M: >215 U/L)
(F: >170 U/L)
2%
3%
Hemoglobin (<8.0 mg/dL)
0%
4%
Hyperglycemia (>250 mg/dL)
2%
1%
Hematuria (>75 RBC/HPF)
3%
2%
Glycosuria (3+)
<1%
1%
Neutrophils (<750/mm3)
3%
5%
Fasting Triglycerides (>750 mg/dL)
4%
2%

Clinical Trials in Pediatric Subjects:

Emtricitabine

In addition to the adverse reactions reported in adults, anemia and hyperpigmentation were observed in 7% and 32%, respectively, of pediatric subjects (3 months to less than 18 years of age) who received treatment with FTC in the larger of two open-label, uncontrolled pediatric trials (N=116).

Tenofovir Disoproxil Fumarate

In pediatric clinical trials (Studies 352 and 321) conducted in 184 HIV 1 infected subjects 2 to less than 18 years of age, the adverse reactions observed in pediatric subjects who received treatment with TDF were consistent with those observed in clinical trials of TDF in adults.

In Study 352 (2 to less than 12 years of age), 89 pediatric subjects received TDF for a median exposure of 104 weeks. Of these, 4 subjects discontinued from the trial due to adverse reactions consistent with proximal renal tubulopathy. Three of these 4 subjects presented with hypophosphatemia and had decreases in total body or spine BMD Z-score [see Warnings and Precautions (5.5)]. Total body BMD gain at Week 48 was less in the TDF group compared to the stavudine (d4T) or zidovudine (AZT) treatment groups. The mean rate of BMD gain in lumbar spine was similar between treatment groups. One TDF-treated subject and none of the d4T- or AZT-treated subjects experienced significant (greater than 4%) lumbar spine BMD loss at Week 48. Changes from baseline in BMD Z-scores were −0.012 for lumbar spine and −0.338 for total body in the 64 subjects who were treated with TDF for 96 weeks.

In Study 321 (12 to less than 18 years of age), the mean rate of BMD gain at Week 48 was less in the TDF compared to the placebo treatment group. Six TDF-treated subjects and one placebo-treated subject had significant (greater than 4%) lumbar spine BMD loss at Week 48. Changes from baseline BMD Z-scores were −0.341 for lumbar spine and −0.458 for total body in the 28 subjects who were treated with TDF for 96 weeks.

In both trials, skeletal growth (height) appeared to be unaffected.

Adverse Reactions from Clinical Trial Experience in Uninfected Subjects Taking Emtricitabine and Tenofovir Disoproxil Fumarate Tablets for HIV-1 PrEP

Clinical Trials in Adult Subjects:

The safety profile of emtricitabine and tenofovir disoproxil fumarate tablets for HIV-1 PrEP was comparable to that observed in clinical trials of HIV-infected subjects based on two randomized placebo-controlled clinical trials (iPrEx, Partners PrEP) in which 2,830 HIV-1 uninfected adults received emtricitabine and tenofovir disoproxil fumarate tablets once daily for HIV-1 PrEP. Subjects were followed for a median of 71 weeks and 87 weeks, respectively. Table 5 provides a list of selected adverse events that occurred in 2% or more of subjects in any treatment group in the iPrEx trial, with an incidence greater than placebo.

Table 5 Selected Adverse Events (All Grades) Reported in 2 % in Any Treatment Group in the iPrEx Trial and Greater than Placebo
FTC/TDF
Placebo
(N=1251)
(N=1248)
Headache
7%
6%
Abdominal pain
4%
2%
Weight decreased
3%
2%

In the Partners PrEP trial, the frequency of adverse events in the emtricitabine and tenofovir disoproxil fumarate tablets treatment group was generally either less than or the same as in the placebo group.

Laboratory Abnormalities: Table 6 provides a list of Grade 2 to 4 laboratory abnormalities observed in the iPrEx and Partners PrEP trials. Six subjects in the TDF-containing arms of the Partners PrEP trial discontinued from the trial due to an increase in serum creatinine compared with no discontinuations in the placebo group. One subject in the emtricitabine and tenofovir disoproxil fumarate tablets arm of the iPrEx trial discontinued from the trial due to an increase in serum creatinine and another subject discontinued due to low serum phosphorus. Grades 2 to 3 proteinuria (2 to 4+) and/or glycosuria (3+) occurred in less than 1% of subjects treated with emtricitabine and tenofovir disoproxil fumarate tablets in the iPrEx trial and Partners PrEP trial.

Table 6 Laboratory Abnormalities (Highest Toxicity Grade Reported for Each Subject) in the iPrEx Trial and Partners PrEP Trial

a.Grading is per DAIDS criteria.

iPrEx Trial
Partners PrEP Trial
Grade 2 to 4a
FTC/TDF (N=1251)
Placebo (N=1248)
FTC/TDF (N=1579)
Placebo (N=1584)
Creatinine (>1.4 ULN)
<1%
<1%
<1%
<1%
Phosphorus (<2.0 mg/dL)
10%
8%
9%
9%
AST (>2.6 ULN)
5%
5%
<1%
<1%
ALT (>2.6 ULN)
7%
7%
<1%
<1%
Hemoglobin (<9.4 mg/dL)
1%
2%
2%
2%
Neutrophils (<750/mm3)
<1%
<1%
5%
3%

Changes in Bone Mineral Density: In clinical trials of HIV-1 uninfected individuals, decreases in BMD were observed. In the iPrEx trial, a substudy of 503 subjects found mean changes from baseline in BMD ranging from –0.4% to –1.0% across total hip, spine, femoral neck, and trochanter in the emtricitabine and tenofovir disoproxil fumarate tablets group compared with the placebo group, which returned toward baseline after discontinuation of treatment. Thirteen percent of emtricitabine and tenofovir disoproxil fumarate tablets-treated subjects versus 6% of placebo- treated subjects lost at least 5% of BMD at the spine during treatment. Bone fractures were reported in 1.7% of the emtricitabine and tenofovir disoproxil fumarate tablets group compared with 1.4% in the placebo group. No correlation between BMD and fractures was noted [see Clinical Studies (14.3)]. The Partners PrEP trial found similar fracture rates between the treatment and placebo groups (0.8% and 0.6%, respectively); no BMD evaluations were performed in this trial [see Clinical Studies (14.4)].

Clinical Trials in Adolescent Subjects

In a single-arm, open-label clinical trial (ATN113), in which 67 HIV-1 uninfected adolescent (15 to 18 years of age) men who have sex with men received emtricitabine and tenofovir disoproxil fumarate tablets once daily for HIV-1 PrEP, the safety profile of emtricitabine and tenofovir disoproxil fumarate tablets was similar to that observed in adults. Median duration to exposure of emtricitabine and tenofovir disoproxil fumarate tablets was 47 weeks [see Use in Specific Populations (8.4)].

In the ATN113 trial, median BMD increased from baseline to Week 48, +2.58% for lumbar spine and +0.72% for total body. One subject had significant (greater than or equal to 4%) total body BMD loss at Week 24. Median changes from baseline BMD Z-scores were 0.0 for lumbar spine and −0.2 for total body at Week 48. Three subjects showed a worsening (change from > −2 to ≤ −2) from baseline in their lumbar spine or total body BMD Z-scores at Week 24 or 48. Interpretation of these data, however, may be limited by the low rate of adherence to emtricitabine and tenofovir disoproxil fumarate tablets by Week 48.

6.2 Postmarketing Experience

The following adverse reactions have been identified during postapproval use of TDF. No additional adverse reactions have been identified during postapproval use of FTC. Because postmarketing reactions are reported voluntarily from a population of uncertain size, it is not always possible to reliably estimate their frequency or establish a causal relationship to drug exposure.

Immune System Disorders

Allergic reaction, including angioedema

Metabolism and Nutrition Disorders

Lactic acidosis, hypokalemia, hypophosphatemia

Respiratory, Thoracic, and Mediastinal Disorders

Dyspnea

Gastrointestinal Disorders

Pancreatitis, increased amylase, abdominal pain

Hepatobiliary Disorders

Hepatic steatosis, hepatitis, increased liver enzymes (most commonly AST, ALT gamma GT)

Skin and Subcutaneous Tissue Disorders

Rash

Musculoskeletal and Connective Tissue Disorders

Rhabdomyolysis, osteomalacia (manifested as bone pain and which may contribute to fractures), muscular weakness, myopathy

Renal and Urinary Disorders

acute renal failure, renal failure, acute tubular necrosis, Fanconi syndrome, proximal renal tubulopathy, interstitial nephritis (including acute cases), nephrogenic diabetes insipidus, renal insufficiency, increased creatinine, proteinuria, polyuria

General Disorders and Administration Site Conditions

Asthenia

The following adverse reactions, listed under the body system headings above, may occur as a consequence of proximal renal tubulopathy: rhabdomyolysis, osteomalacia, hypokalemia, muscular weakness, myopathy, hypophosphatemia.

DRUG INTERACTIONS

7.1 Drugs Affecting Renal Function

FTC and tenofovir are primarily excreted by the kidneys by a combination of glomerular filtration and active tubular secretion [see Clinical Pharmacology (12.3)]. No drug-drug interactions due to competition for renal excretion have been observed; however, coadministration of emtricitabine and tenofovir disoproxil fumarate tablets with drugs that are eliminated by active tubular secretion may increase concentrations of FTC, tenofovir, and/or the coadministered drug. Some examples include, but are not limited to, acyclovir, adefovir dipivoxil, cidofovir, ganciclovir, valacyclovir, valganciclovir, aminoglycosides (e.g., gentamicin), and high-dose or multiple NSAIDs [see Warnings and Precautions (5.3)]. Drugs that decrease renal function may increase concentrations of FTC and/or tenofovir.

7.2 Established and Significant Interactions

Table 7 provides a listing of established or clinically significant drug interactions. The drug interactions described are based on studies conducted with either emtricitabine and tenofovir disoproxil fumarate, the components of emtricitabine and tenofovir disoproxil fumarate tablets (FTC and TDF) as individual agents and/or in combination, or are predicted drug interactions that may occur with emtricitabine and tenofovir disoproxil fumarate tablets [see Clinical Pharmacology (12.3)].

Table 7 Established and Significanta Drug Interactions: Alteration in Dose or Regimen May Be Recommended Based on Drug Interaction Trials

a.This table is not all inclusive.

b.↑=Increase, ↓=Decrease

c.Indicates that a drug-drug interaction trial was conducted.

USE IN SPECIFIC POPULATIONS

8.1 Pregnancy

Teratogenic Effects

Pregnancy Exposure Registry:

There is a pregnancy exposure registry that monitors pregnancy outcomes in women exposed to emtricitabine and tenofovir disoproxil fumarate tablets during pregnancy. Healthcare providers are encouraged to register patients by calling the Antiretroviral Pregnancy Registry (APR) at 1-800-258-4263.

Risk Summary

Data on the use of emtricitabine and tenofovir disoproxil fumarate tablets during pregnancy from observational studies have shown no increased risk of major birth defects. Available data from the APR show no significant difference in the overall risk of major birth defects with first trimester exposure for emtricitabine (FTC) (2.3%) or tenofovir disoproxil fumarate (TDF) (2.1%) compared with the background rate for major birth defects of 2.7% in a U.S. reference population of the Metropolitan Atlanta Congenital Defects Program (MACDP) (see Data). The rate of miscarriage for individual drugs is not reported in the APR. In the U.S. general population, the estimated background risk of miscarriage in clinically recognized pregnancies is 15 to 20%.

In animal reproduction studies, no adverse developmental effects were observed when the components of emtricitabine and tenofovir disoproxil fumarate tablets were administered separately at doses/exposures ≥60 (FTC), ≥14 (TDF) and 2.7 (tenofovir) times those of the recommended daily dose of emtricitabine and tenofovir disoproxil fumarate tablets (see Data).

Clinical Considerations

Disease-Associated Maternal and/or Embryo/Fetal Risk:

HIV-1 PrEP

Published studies indicate an increased risk of HIV-1 infection during pregnancy and an increased risk of mother to child transmission during acute HIV-1 infection. In women at risk of acquiring HIV-1, consideration should be given to methods to prevent acquisition of HIV, including continuing or initiating emtricitabine and tenofovir disoproxil fumarate tablets for HIV-1 PrEP, during pregnancy.

Data

Human Data:

Emtricitabine and tenofovir disoproxil fumarate tablets for HIV-1 PrEP

In an observational study based on prospective reports to the APR, 78 HIV-seronegative women exposed to emtricitabine and tenofovir disoproxil fumarate tablets during pregnancy delivered live-born infants with no major malformations. All but one were first trimester exposures, and the median duration of exposure was 10.5 weeks. There were no new safety findings in the women receiving emtricitabine and tenofovir disoproxil fumarate tablets for HIV-1 PrEP compared with HIV-1 infected women treated with other antiretroviral medications.

Emtricitabine

Based on prospective reports to the APR of exposures to FTC-containing regimens during pregnancy resulting in live births (including over 3,300 exposed in the first trimester and over 1,300 exposed in the second/third trimester), the prevalence of major birth defects in live births was 2.6% (95% CI: 2.1% to 3.2%) and 2.3% (95% CI: 1.6% to 3.3%) following first and second/third trimester exposure, respectively to FTC-containing regimens.

Tenofovir Disoproxil Fumarate

Based on prospective reports to the APR of exposures to TDF-containing regimens during pregnancy resulting in live births (including over 4,000 exposed in the first trimester and over 1,700 exposed in the second/third trimester), the prevalence of major birth defects in live births was 2.4% (95% CI: 2.0% to 2.9%) and 2.4% (95% CI: 1.7% to 3.2%) following first and second/third trimester exposure, respectively to TDF-containing regimens.

Methodologic limitations of the APR include the use of MACDP as the external comparator group. The MACDP population is not disease-specific, evaluates women and infants from a limited geographic area, and does not include outcomes for births that occurred at <20 weeks gestation.

Additionally, published observational studies on emtricitabine and tenofovir exposure in pregnancy have not shown an increased risk for major malformations.

Animal Data:

Emtricitabine

FTC was administered orally to pregnant mice (at 0, 250, 500, or 1,000 mg/kg/day), and rabbits (at 0, 100, 300, or 1,000 mg/kg/day) through organogenesis (on gestation days 6 through 15, and 7 through 19, respectively). No significant toxicological effects were observed in embryo-fetal toxicity studies performed with FTC in mice at exposures (AUC) approximately 60 times higher and in rabbits at approximately 120 times higher than human exposures at the recommended daily dose. In a pre/postnatal development study in mice, FTC was administered orally at doses up to 1,000 mg/kg/day; no significant adverse effects directly related to drug were observed in the offspring exposed daily from before birth (in utero) through sexual maturity at daily exposures (AUC) of approximately 60 times higher than human exposures at the recommended daily dose.

Tenofovir Disoproxil Fumarate

TDF was administered orally to pregnant rats (at 0, 50, 150, or 450 mg/kg/day) and rabbits (at 0, 30, 100, or 300 mg/kg/day) through organogenesis (on gestation days 7 through 17, and 6 through 18, respectively). No significant toxicological effects were observed in embryo-fetal toxicity studies performed with TDF in rats at doses up to 14 times the human dose based on body surface area comparisons and in rabbits at doses up to 19 times the human dose based on body surface area comparisons. In a pre/postnatal development study in rats, TDF was administered orally through lactation at doses up to 600 mg/kg/day; no adverse effects were observed in the offspring at tenofovir exposures of approximately 2.7 times higher than human exposures at the recommended daily dose of emtricitabine and tenofovir disoproxil fumarate tablets.

8.2 Lactation

Risk Summary

Based on published data, FTC and tenofovir have been shown to be present in human breast milk (see Data). It is not known if the components of emtricitabine and tenofovir disoproxil fumarate tablets affect milk production or have effects on the breastfed child.

Treatment of HIV-1 Infection:

The Centers for Disease Control and Prevention recommend that HIV-1 infected mothers not breastfeed their infants to avoid risking postnatal transmission of HIV-1.

Because of the potential for: (1) HIV transmission (in HIV-negative infants); (2) developing viral resistance (in HIV-positive infants); and (3) adverse reactions in a breastfed infant similar to those seen in adults, instruct mothers not to breastfeed if they are taking emtricitabine and tenofovir disoproxil fumarate tablets for the treatment of HIV-1.

HIV-1 PrEP:

In HIV-uninfected women, the developmental and health benefits of breastfeeding and the mother's clinical need for emtricitabine and tenofovir disoproxil fumarate tablets for HIV-1 PrEP should be considered along with any potential adverse effects on the breastfed child from emtricitabine and tenofovir disoproxil fumarate tablets and the risk of HIV-1 acquisition due to nonadherence and subsequent mother to child transmission.

Women should not breastfeed if acute HIV-1 infection is suspected because of the risk of HIV-1 transmission to the infant.

Data

HIV-1 PrEP: In a study of 50 breastfeeding women who received emtricitabine and tenofovir disoproxil fumarate tablets for HIV-1 PrEP between 1 and 24 weeks postpartum (median 13 weeks), after 7 days of treatment, tenofovir was undetectable but FTC was detectable in the plasma of most infants. In these infants, the average FTC plasma concentration was less than 1% of the FTC Cmax observed in HIV-infected infants (up to 3 months of age) receiving the therapeutic dose of FTC (3 mg/kg/day). There were no serious adverse events. Two infants (4%) had an adverse event of mild diarrhea which resolved.

8.4 Pediatric Use

Treatment of HIV-1 Infection

No pediatric clinical trial was conducted to evaluate the safety and efficacy of emtricitabine and tenofovir disoproxil fumarate tablets in patients with HIV-1 infection. Data from previously conducted trials with the individual drug products, FTC and TDF, were relied upon to support dosage recommendations for emtricitabine and tenofovir disoproxil fumarate tablets. For additional information, consult the prescribing information for EMTRIVA and VIREAD.

Emtricitabine and tenofovir disoproxil fumarate tablets should only be administered to HIV-1 infected pediatric patients with body weight greater than or equal to 17 kg and who are able to swallow a tablet. Because it is a fixed-dose combination tablet, emtricitabine and tenofovir disoproxil fumarate tablets cannot be adjusted for patients of lower weight [see Warnings and Precautions (5.5), Adverse Reactions (6.1) and Clinical Pharmacology (12.3)]. Emtricitabine and tenofovir disoproxil fumarate tablets are not approved for use in pediatric patients weighing less than 17 kg.

HIV-1 PrEP

The safety and effectiveness of emtricitabine and tenofovir disoproxil fumarate tablets for HIV-1 PrEP in at-risk adolescents weighing at least 35 kg is supported by data from adequate and well-controlled studies of emtricitabine and tenofovir disoproxil fumarate tablets for HIV-1 PrEP in adults with additional data from safety and pharmacokinetic studies in previously conducted trials with the individual drug products, FTC and TDF, in HIV-1 infected adults and pediatric subjects [see Dosage and Administration (2.5), Adverse Reactions (6.1), Clinical Pharmacology (12.3 and 12.4),and Clinical Studies (14.3 and 14.4)].

Safety, adherence, and resistance were evaluated in a single-arm, open-label clinical trial (ATN113) in which 67 HIV-1 uninfected at-risk adolescent men who have sex with men received emtricitabine and tenofovir disoproxil fumarate tablets once daily for HIV-1 PrEP. The mean age of subjects was 17 years (range 15 to 18 years); 46% were Hispanic, 52% Black, and 37% White. The safety profile of emtricitabine and tenofovir disoproxil fumarate tablets in ATN113 was similar to that observed in the adult HIV-1 PrEP trials [see Adverse Reactions (6.1)].

In the ATN113 trial, HIV-1 seroconversion occurred in 3 subjects. Tenofovir diphosphate levels in dried blood spot assays indicate that these subjects had poor adherence. No tenofovir- or FTC- associated HIV-1 resistance substitutions were detected in virus isolated from the 3 subjects who seroconverted [see Microbiology (12.4)].

Adherence to study drug, as demonstrated by tenofovir diphosphate levels in dried blood spot assays, declined markedly after Week 12 once subjects switched from monthly to quarterly visits, suggesting that adolescents may benefit from more frequent visits and counseling [see Warnings and Precautions (5.2)].

Safety and effectiveness of emtricitabine and tenofovir disoproxil fumarate tablets for HIV-1 PrEP in pediatric patients weighing less than 35 kg have not been established.

8.5 Geriatric Use

Clinical trials of FTC, TDF, or emtricitabine and tenofovir disoproxil fumarate tablets did not include sufficient numbers of subjects aged 65 and over to determine whether they respond differently from younger subjects.

8.6 Renal Impairment

Treatment of HIV-1 Infection

The dosing interval for emtricitabine and tenofovir disoproxil fumarate tablets should be modified in HIV-infected adult individuals with estimated creatinine clearance of 30 to 49 mL/min. emtricitabine and tenofovir disoproxil fumarate tablets are not recommended in individuals with estimated creatinine clearance below 30 mL/min and in individuals with end-stage renal disease requiring dialysis [see Dosage and Administration (2.6)].

HIV-1 PrEP

Emtricitabine and tenofovir disoproxil fumarate tablets for HIV-1 PrEP are not recommended in HIV-1 uninfected individuals with estimated creatinine clearance below 60 mL/min. If a decrease in estimated creatinine clearance is observed in uninfected individuals while using emtricitabine and tenofovir disoproxil fumarate tablets for HIV-1 PrEP, evaluate potential causes and re-assess potential risks and benefits of continued use [see Dosage and Administration (2.6)].

DESCRIPTION

Emtricitabine and tenofovir disoproxil fumarate tablets are fixed-dose combination tablets containing emtricitabine (FTC) and tenofovir disoproxil fumarate (TDF). FTC is a synthetic nucleoside analog of cytidine. TDF is converted in vivo to tenofovir, an acyclic nucleoside phosphonate (nucleotide) analog of adenosine 5'-monophosphate. Both FTC and tenofovir exhibit inhibitory activity against HIV-1 reverse transcriptase.

Emtricitabine

The chemical name of FTC is 5-fluoro-1-(2R,5S)-[2-(hydroxymethyl)-1,3-oxathiolan-5 yl]cytosine. FTC is the (-) enantiomer of a thio analog of cytidine, which differs from other cytidine analogs in that it has a fluorine in the 5-position.

It has a molecular formula of C8H10FN3O3S and a molecular weight of 247.24. It has the following structural formula:

[Image]

FTC is a white to off-white colored powder with a solubility of approximately 112 mg/mL in water at 25 C. The partition coefficient (log p) for emtricitabine is -0.43 and the pKa is 2.65.

Tenofovir Disoproxil Fumarate

TDF is a fumaric acid salt of the bis-isopropoxycarbonyloxymethyl ester derivative of tenofovir. The chemical name of tenofovir DF is 9-[(R)-2 [[bis[[(isopropoxycarbonyl)oxy]- methoxy]phosphinyl]methoxy]propyl]adenine fumarate (1:1). It has a molecular formula of C19H30N5O10P • C4H4O4 and a molecular weight of 635.51. It has the following structural formula:

[Image]

Tenofovir disoproxil fumarate is a white to off-white crystalline powder with a solubility of 9.78 mg/mL in water at 25 C. The partition coefficient (log p) for tenofovir disoproxil is 1.25 and the pKa is 3.75. All dosages are expressed in terms of TDF except where otherwise noted.

Emtricitabine and tenofovir disoproxil fumarate tablets are for oral administration, and are available in the following strengths:

Film-coated tablet containing 200 mg of FTC and 300 mg of TDF (which is equivalent to 245 mg of tenofovir disoproxil) as active ingredients

Emtricitabine and tenofovir disoproxil fumarate tablets also include the following inactive ingredients: colloidal silicon dioxide, croscarmellose sodium, magnesium stearate, mannitol and microcrystalline cellulose. The tablets are coated with Opadry II White 32K180001, which contains hypromellose 2910, lactose monohydrate, titanium dioxide and triacetin.

HOW SUPPLIED

Emtricitabine and tenofovir disoproxil fumarate tablets are available in bottles containing 30 and 100 tablets with child-resistant closure as follows:

200 mg of FTC and 300 mg of TDF (equivalent to 245 mg of tenofovir disoproxil) tablets are white, capsule shaped, biconvex, film-coated, debossed with "LU" on one side and "Q31" on the other side.

Bottles of 30
68180-287-06
Bottles of 100
68180-287-01

Store at 25 C (77 F); excursions permitted to 15º to 30 C (59 to 86 F) [See USP Controlled Room Temperature].

Keep container tightly closed
Dispense only in original container

PATIENT COUNSELING INFORMATION

Advise the patient to read the FDA-approved patient labeling (Medication Guide).

Important Information for Uninfected Individuals Taking Emtricitabine and Tenofovir Disoproxil Fumarate Tablets for HIV-1 PrEP

Advise HIV-uninfected individuals about the following [see Warnings and Precautions (5.2)]:

The need to confirm that they are HIV-negative before starting to take emtricitabine and tenofovir disoproxil fumarate tablets to reduce the risk of acquiring HIV-1.
That HIV-1 resistance substitutions may emerge in individuals with undetected HIV-1 infection who are taking emtricitabine and tenofovir disoproxil fumarate tablets, because emtricitabine and tenofovir disoproxil fumarate tablets alone does not constitute a complete regimen for HIV-1 treatment.
The importance of taking emtricitabine and tenofovir disoproxil fumarate tablets on a regular dosing schedule and strict adherence to the recommended dosing schedule to reduce the risk of acquiring HIV-1. Uninfected individuals who miss doses are at greater risk of acquiring HIV-1 than those who do not miss doses.
That emtricitabine and tenofovir disoproxil fumarate tablets does not prevent other sexually acquired infections and should only be used as part of a complete prevention strategy including other prevention measures.
To use condoms consistently and correctly to lower the chances of sexual contact with any body fluids such as semen, vaginal secretions, or blood.
The importance of knowing their HIV-1 status and the HIV-1 status of their partner(s).
The importance of virologic suppression in their partner(s) with HIV-1.
The need to get tested regularly for HIV-1 (at least every 3 months, or more frequently for some individuals such as adolescents) and to ask their partner(s) to get tested as well.
To report any symptoms of acute HIV-1 infection (flu-like symptoms) to their healthcare provider immediately.
That the signs and symptoms of acute infection include fever, headache, fatigue, arthralgia, vomiting, myalgia, diarrhea, pharyngitis, rash, night sweats, and adenopathy (cervical and inguinal).
To get tested for other sexually transmitted infections, such as syphilis, chlamydia, and gonorrhea, that may facilitate HIV-1 transmission.
To assess their sexual risk behavior and get support to help reduce sexual risk behavior.

Severe Acute Exacerbation of Hepatitis B in Patients Infected with HBV

Inform individuals that severe acute exacerbations of hepatitis B have been reported in patients who are infected with HBV and have discontinued emtricitabine and tenofovir disoproxil fumarate tablets [see Warnings and Precautions (5.1)]. Advise HBV-infected individuals to not discontinue emtricitabine and tenofovir disoproxil fumarate tablets without first informing their healthcare provider.

New Onset or Worsening Renal Impairment

Inform HIV-1 infected patients and uninfected individuals that renal impairment, including cases of acute renal failure and Fanconi syndrome, has been reported in association with the use of TDF, a component of emtricitabine and tenofovir disoproxil fumarate tablets. Advise patients to avoid emtricitabine and tenofovir disoproxil fumarate tablets with concurrent or recent use of a nephrotoxic agent (e.g., high-dose or multiple NSAIDs) [see Warnings and Precautions (5.3)]. The dosing interval of emtricitabine and tenofovir disoproxil fumarate tablets may need adjustment in HIV-1 infected patients with renal impairment. emtricitabine and tenofovir disoproxil fumarate tablets for HIV-1 PrEP should not be used in HIV-1 uninfected individuals if estimated creatinine clearance is less than 60 mL/min. If a decrease in estimated creatinine clearance is observed in uninfected individuals while using emtricitabine and tenofovir disoproxil fumarate tablets for HIV-1 PrEP, evaluate potential causes and re-assess potential risks and benefits of continued use [see Dosage and Administration (2.6)].

Immune Reconstitution Syndrome

Inform HIV-1 infected patients that in some patients with advanced HIV infection (AIDS), signs and symptoms of inflammation from previous infections may occur soon after anti-HIV treatment is started. It is believed that these symptoms are due to an improvement in the body's immune response, enabling the body to fight infections that may have been present with no obvious symptoms. Advise patients to inform their healthcare provider immediately of any symptoms of infection [see Warnings and Precautions (5.4)].

Bone Loss and Mineralization Defects

Inform patients that decreases in bone mineral density have been observed with the use of TDF or emtricitabine and tenofovir disoproxil fumarate tablets. Consider bone monitoring in patients and uninfected individuals who have a history of pathologic bone fracture or at risk for osteopenia [see Warnings and Precautions (5.5)].

Lactic Acidosis and Severe Hepatomegaly

Inform HIV-1 infected patients and uninfected individuals that lactic acidosis and severe hepatomegaly with steatosis, including fatal cases, have been reported. Treatment with emtricitabine and tenofovir disoproxil fumarate tablets should be suspended in any person who develops clinical symptoms suggestive of lactic acidosis or pronounced hepatotoxicity [see Warnings and Precautions (5.6)].

Drug Interactions

Advise individuals that emtricitabine and tenofovir disoproxil fumarate tablets may interact with many drugs; therefore, advise individuals to report to their healthcare provider the use of any other medication, including other HIV drugs and drugs for treatment of hepatitis C virus [see Warnings and Precautions (5.7) and Drug Interactions (7)].

Dosage Recommendations for Treatment of HIV-1 Infection

Inform HIV-1 infected patients that it is important to take emtricitabine and tenofovir disoproxil fumarate tablets with other antiretroviral drugs for the treatment of HIV-1 on a regular dosing schedule with or without food and to avoid missing doses as it can result in development of resistance.

Pregnancy Registry

Inform individuals using emtricitabine and tenofovir disoproxil fumarate tablets for HIV-1 treatment or HIV-1 PrEP that there is an antiretroviral pregnancy registry to monitor fetal outcomes of pregnant women exposed to emtricitabine and tenofovir disoproxil fumarate tablets [see Use in Specific Populations (8.1)].

Lactation

Instruct mothers not to breastfeed if they are taking emtricitabine and tenofovir disoproxil fumarate tablets for the treatment of HIV-1 infection or if acute HIV-1 infection is suspected in a mother taking emtricitabine and tenofovir disoproxil fumarate tablets for HIV-1 PrEP because of the risk of passing the HIV-1 virus to the baby. In HIV-uninfected women, the benefits and risks of emtricitabine and tenofovir disoproxil fumarate tablets while breastfeeding should be evaluated, including the risk of HIV-1 acquisition due to medication nonadherence and subsequent mother to child transmission [see Use in Specific Populations (8.2)].

The brands listed are trademarks of their respective owners and are not trademarks of Lupin Pharmaceuticals, Inc. The makers of these brands are not affiliated with and do not endorse Lupin Pharmaceuticals, Inc. or its products.

Manufactured for:

Lupin Pharmaceuticals, Inc.

Baltimore, Maryland 21202

United States

MADE IN INDIA

Revised: December 2020

Medication Guide

Emtricitabine and Tenofovir Disoproxil Fumarate

(EM-trye-SYE-ta-been and ten-OF-oh-vir DYE-soe-PROX-il FUE-ma-rate)

Tablets

Read this Medication Guide before you start taking emtricitabine and tenofovir disoproxil fumarate tablets and each time you get a refill. There may be new information. This information does not take the place of talking to your healthcare provider about your medical condition or your treatment.

This Medication Guide provides information about two different ways that emtricitabine and tenofovir disoproxil fumarate tablets may be used. See the section "What is emtricitabine and tenofovir disoproxil fumarate tablet?" for detailed information about how emtricitabine and tenofovir disoproxil fumarate tablets may be used.

What is the most important information I should know about emtricitabine and tenofovir disoproxil fumarate tablets?

Emtricitabine and tenofovir disoproxil fumarate tablets can cause serious side effects, including:

Worsening of hepatitis B virus infection (HBV). Your healthcare provider will test you for HBV before start or when you start treatment with emtricitabine and tenofovir disoproxil fumarate tablets. If you have HBV infection and take emtricitabine and tenofovir disoproxil fumarate tablets, your HBV may get worse (flare-up) if you stop taking emtricitabine and tenofovir disoproxil fumarate tablets. A "flare-up" is when your HBV infection suddenly returns in a worse way than before.

Do not run out of emtricitabine and tenofovir disoproxil fumarate tablets. Refill your prescription or talk to your healthcare provider before your emtricitabine and tenofovir disoproxil fumarate tablets are all gone.
Do not stop taking emtricitabine and tenofovir disoproxil fumarate tablets without first talking to your healthcare provider.
If you stop taking emtricitabine and tenofovir disoproxil fumarate tablets, your healthcare provider will need to check your health often and do blood tests regularly for several months to check your HBV infection, or give you a medicine to treat hepatitis B. Tell your healthcare provider about any new or unusual symptoms you may have after you stop taking emtricitabine and tenofovir disoproxil fumarate tablets.

For more information about side effects, see the section "What are the possible side effects of emtricitabine and tenofovir disoproxil fumarate tablets?".

Other important information for people who take emtricitabine and tenofovir disoproxil fumarate tablets to help reduce their risk of getting human immunodeficiency virus-1 (HIV-1) infection, also called pre-exposure prophylaxis or "PrEP":

Before taking emtricitabine and tenofovir disoproxil fumarate tablets to reduce your risk of getting HIV-1:

You must be HIV-1 negative to start emtricitabine and tenofovir disoproxil fumarate tablets. You must get tested to make sure that you do not already have HIV-1 infection.
Do not take emtricitabine and tenofovir disoproxil fumarate tablets for HIV-1 PrEP unless you are confirmed to be HIV-1 negative.
Some HIV-1 tests can miss HIV-1 infection in a person who has recently become infected. If you have flu-like symptoms, you could have recently become infected with HIV-1. Tell your healthcare provider if you had a flu-like illness within the last month before starting emtricitabine and tenofovir disoproxil fumarate tablets or at any time while taking emtricitabine and tenofovir disoproxil fumarate tablets. Symptoms of new HIV 1 infection include:

tiredness
fever
joint or muscle aches
headache
sore throat
vomiting or diarrhea
rash
night sweats
enlarged lymph nodes in the neck or groin

While you are taking emtricitabine and tenofovir disoproxil fumarate tablets for HIV-1 PrEP:

Emtricitabine and tenofovir disoproxil fumarate tablets does not prevent other sexually transmitted infections (STIs). Practice safer sex by using a latex or polyurethane condom to reduce the risk of getting STIs.
You must stay HIV-negative to keep taking emtricitabine and tenofovir disoproxil fumarate tablets for HIV-1 PrEP.

Know your HIV-1 status and the HIV-1 status of your partners.
Ask your partners with HIV-1 if they are taking anti-HIV-1 medicines and have an undetectable viral load. An undetectable viral load is when the amount of virus in the blood is too low to be measured in a lab test. To maintain an undetectable viral load, your partners must keep taking HIV-1 medicines every day. Your risk of getting HIV-1 is lower if your partners with HIV-1 are taking effective treatment.
Get tested for HIV-1 at least every 3 months or when your healthcare provider tells you.
Get tested for other STIs such as syphilis, chlamydia, and gonorrhea. These infections make it easier for HIV-1 to infect you.
If you think you were exposed to HIV-1, tell your healthcare provider right away. They may want to do more tests to be sure you are still HIV-1 negative.
Get information and support to help reduce sexual risk rbehaviors.
Do not miss any doses of emtricitabine and tenofovir disoproxil fumarate tablets. Missing doses increases your risk of getting HIV-1 infection.

If you do become HIV-1 positive, you need more medicine than emtricitabine and tenofovir disoproxil fumarate tablets alone to treat HIV-1. Emtricitabine and tenofovir disoproxil fumarate tablets by itself is not a complete treatment for HIV-1.

If you have HIV-1 and take only emtricitabine and tenofovir disoproxil fumarate tablets, over time your HIV-1 may become harder to treat.

What are emtricitabine and tenofovir disoproxil fumarate tablets?

Emtricitabine and tenofovir disoproxil fumarate tablet is a prescription medicine that may be used in two different ways. Emtricitabine and tenofovir disoproxil fumarate tablet is used:

to treat HIV-1 infection when used with other anti-HIV-1 medicines in adults and children who weigh at least 37 pounds (at least 17 kg).
for HIV-1 PrEP to reduce the risk of getting HIV-1 infection in adults and adolescents who weigh at least 77 pounds (at least 35 kg).

HIV-1 is the virus that causes Acquired Immune Deficiency Syndrome(AIDS).

Emtricitabine and tenofovir disoproxil fumarate tablets contains the medicines emtricitabine and tenofovir disoproxil fumarate.

It is not known if emtricitabine and tenofovir disoproxil fumarate tablets for treatment of HIV-1 infection are safe and effective in children who weigh less than 37 pounds (17 kg).

It is not known if emtricitabine and tenofovir disoproxil fumarate tablets are safe and effective in reducing the risk of HIV-1 infection in people who weigh less than 77 pounds (35 kg)

For people taking emtricitabine and tenofovir disoproxil fumarate tablets for HIV-1 PrEP:

Do not take emtricitabine and tenofovir disoproxil fumarate tablets for HIV-1 PrEP if:

you already have HIV-1 infection . If you are HIV-1 positive, you need to take other medicines with emtricitabine and tenofovir disoproxil fumarate tablets to treat HIV-1. Emtricitabine and tenofovir disoproxil fumarate tablet by itself is not a complete treatment for HIV-1.
you do not know your HIV-1 infection status . You may already be HIV-1 positive. You need to take other HIV-1 medicines with emtricitabine and tenofovir disoproxil fumarate tablets to treat HIV-1.

Emtricitabine and tenofovir disoproxil fumarate tablets can only help reduce your risk of getting HIV-1 before you are infected.

What should I tell my healthcare provider before taking emtricitabine and tenofovir disoproxil fumarate tablets?

Before taking emtricitabine and tenofovir disoproxil fumarate tablets, tell your healthcare provider about all of your medical conditions, including if you:

have liver problems, including HBV infection
have kidney problems or receive kidney dialysis treatment
have bone problems
are pregnant or plan to become pregnant. It is not known if emtricitabine and tenofovir disoproxil fumarate tablets can harm your unborn baby. Tell your healthcare provider if you become pregnant during treatment with emtricitabine and tenofovir disoproxil fumarate tablets.

Pregnancy Registry: There is a pregnancy registry for people who take emtricitabine and tenofovir disoproxil fumarate tablets during pregnancy. The purpose of this registry is to collect information about the health of you and your baby. Talk with your healthcare provider about how you can take part in this registry.

are breastfeeding or plan to breastfeed. Emtricitabine and tenofovir disoproxil fumarate can pass to your baby in your breast milk.

Do not breastfeed if you have HIV-1 or if you think you have recently become infected with HIV-1 because of the risk of passing HIV-1 to your baby.
If you take emtricitabine and tenofovir disoproxil fumarate tablets for HIV-1 PrEP, talk with your healthcare provider about the best way to feed your baby.

Tell your healthcare provider about all the medicines you take, including prescription and over-the-counter medicines, vitamins, and herbal supplements.

Some medicines may interact with emtricitabine and tenofovir disoproxil fumarate tablets. Keep a list of your medicines and show it to your healthcare provider and pharmacist when you get a new medicine.

You can ask your healthcare provider or pharmacist for a list of medicines that interact with emtricitabine and tenofovir disoproxil fumarate tablets.
Do not start a new medicine without telling your healthcare provider. Your healthcare provider can tell you if it is safe to take emtricitabine and tenofovir disoproxil fumarate tablets with other medicines.

How should I take emtricitabine and tenofovir disoproxil fumarate tablets?

Take emtricitabine and tenofovir disoproxil fumarate tablets exactly as your healthcare provider tells you to take it.
If you take emtricitabine and tenofovir disoproxil fumarate tablets to treat HIV-1 infection, you need to take other HIV-1 medicines. Your healthcare provider will tell you what medicines to take and how to take them.
Take emtricitabine and tenofovir disoproxil fumarate tablets 1 time each day with or without food.
Do not change your dose or stop taking emtricitabine and tenofovir disoproxil fumarate tablets without first talking with your healthcare provider. Stay under a healthcare provider's care when taking emtricitabine and tenofovir disoproxil fumarate tablets. Do not miss a dose of emtricitabine and tenofovir disoproxil fumarate tablets.
If you take too much emtricitabine and tenofovir disoproxil fumarate tablets, call your healthcare provider or go to the nearest hospital emergency room right away.
When your emtricitabine and tenofovir disoproxil fumarate tablets supply starts to run low, get more from your healthcare provider or pharmacy.

If you are taking emtricitabine and tenofovir disoproxil fumarate tablets for treatment of HIV-1, the amount of virus in your blood may increase if the medicine is stopped for even a short time. The virus may develop resistance to emtricitabine and tenofovir disoproxil fumarate tablets and become harder to treat.
If you are taking emtricitabine and tenofovir disoproxil fumarate tablets for HIV-1 PrEP, missing doses increases your risk of getting HIV-1 infection.

What are the possible side effects of emtricitabine and tenofovir disoproxil fumarate tablets?

Emtricitabine and tenofovir disoproxil fumarate tablets may cause serious side effects, including:

See "What is the most important information I should know about emtricitabine and tenofovir disoproxil fumarate tablets?"
New or worse kidney problems, including kidney failure . Your healthcare provider should do blood and urine tests to check your kidneys before you start and during treatment with emtricitabine and tenofovir disoproxil fumarate tablets. Your healthcare provider may tell you to take emtricitabine and tenofovir disoproxil fumarate tablets less often, or to stop taking emtricitabine and tenofovir disoproxil fumarate tablets if you get new or worse kidney problems.
Changes in your immune system (Immune Reconstitution Syndrome) can happen when taking medicines to treat HIV-1 infection. Your immune system may get stronger and begin to fight infections that have been hidden in your body for a long time. Tell your healthcare provider right away if you start having any new symptoms after starting your HIV-1 medicine.
Bone problems can happen in some people who take emtricitabine and tenofovir disoproxil fumarate tablets. Bone problems include bone pain, or softening or thinning of bones, which may lead to fractures. Your healthcare provider may need to do tests to check your bones.
Too much lactic acid in your blood (lactic acidosis). Too much lactic acid is a serious but rare medical emergency that can lead to death. Tell your healthcare provider right away if you get these symptoms: weakness or being more tired than usual, unusual muscle pain, being short of breath or fast breathing, stomach pain with nausea and vomiting, cold or blue hands and feet, feel dizzy or lightheaded, or a fast or abnormal heartbeat.
Severe liver problems . In rare cases, severe liver problems can happen that can lead to death. Tell your healthcare provider right away if you get these symptoms : skin or the white part of your eyes turns yellow, dark "tea-colored" urine, light-colored stools, loss of appetite for several days or longer, nausea, or stomach-area pain.

The most common side effects of emtricitabine and tenofovir disoproxil fumarate tablets for treatment of HIV-1 include:

Diarrhea
depression
nausea
problems sleeping
tiredness
abnormal dreams
headache
rash
dizziness

Common side effects in people who take emtricitabine and tenofovir disoproxil fumarate tablets for HIV-1 PrEP include:

• headache • stomach-area (abdomen) pain • decreased weight

These are not all the possible side effects of emtricitabine and tenofovir disoproxil fumarate tablets.

Call your doctor for medical advice about side effects. You may report side effects to FDA at 1-800-FDA-1088.

How should I store emtricitabine and tenofovir disoproxil fumarate tablets?

Store emtricitabine and tenofovir disoproxil fumarate tablets at room temperature between 68 F to 77 F (20 C to 25 C).
Keep emtricitabine and tenofovir disoproxil fumarate tablets in its original container.
Keep the container tightly closed.
Do not use emtricitabine and tenofovir disoproxil fumarate tablets if seal over bottle opening is broken or missing.

Keep emtricitabine and tenofovir disoproxil fumarate tablets and all other medicines out of reach of children.

General information about emtricitabine and tenofovir disoproxil fumarate tablets.

Medicines are sometimes prescribed for purposes other than those listed in a Medication Guide. Do not use emtricitabine and tenofovir disoproxil fumarate tablets for a condition for which it was not prescribed. Do not give emtricitabine and tenofovir disoproxil fumarate tablets to other people, even if they have the same symptoms you have. It may harm them. You can ask your healthcare provider or pharmacist for information about emtricitabine and tenofovir disoproxil fumarate tablets that is written for health professionals.

What are the ingredients in emtricitabine and tenofovir disoproxil fumarate tablets?

Active ingredients: emtricitabine and tenofovir disoproxil fumarate.

Inactive ingredients: colloidal silicon dioxide, croscarmellose sodium, magnesium stearate, mannitol and microcrystalline cellulose. The tablets are coated with Opadry II White 32K180001, which contains hypromellose 2910, lactose monohydrate, titanium dioxide and triacetin.

The brands listed are trademarks of their respective owners and are not trademarks of Lupin Pharmaceuticals, Inc. The makers of these brands are not affiliated with and do not endorse Lupin Pharmaceuticals, Inc. or its products.

This Medication Guide has been approved by the U.S. Food and Drug Administration

Manufactured for:

Lupin Pharmaceuticals, Inc.

Baltimore, Maryland 21202

United States

MADE IN INDIA

Revised: December 2020